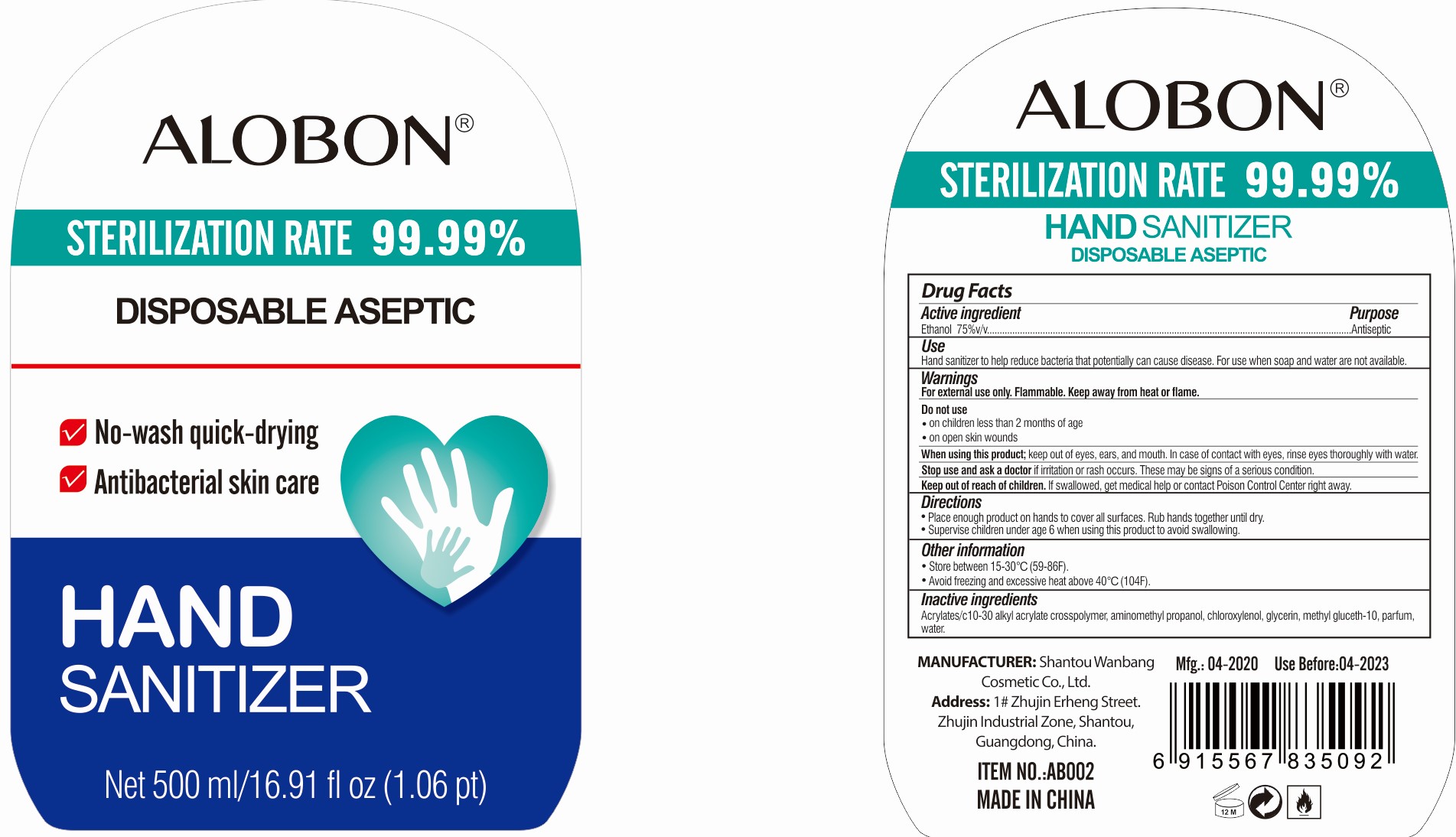 DRUG LABEL: ALOBON Hand Sanitizer
NDC: 78692-134 | Form: GEL
Manufacturer: Shantou Wanbang Cosmetic Co., Ltd
Category: otc | Type: HUMAN OTC DRUG LABEL
Date: 20200709

ACTIVE INGREDIENTS: ALCOHOL 75 mL/100 mL
INACTIVE INGREDIENTS: CHLOROXYLENOL; GLYCERIN; METHYL GLUCETH-10; WATER; AMINOMETHYLPROPANOL; CARBOMER INTERPOLYMER TYPE A (55000 CPS)

Active Ingredient

Ethanol 75%v/v

Purpose

Antiseptic

Use

Hand sanitizer to help reduce bacteria that potentially can cause disease. For use when soap and water are not available.

Warnings

For external use only. Flammable. Keep away from heat or flame.

Do not use

- on children less than 2 months of age
- on open skin wounds

When using this product; keep out of eyes, ears, and mouth. In case of contact with eyes, rinse eyes thoroughly with water.

Stop use and ask a doctor if irritation or rash occurs. These may be signs of a serious condition.

Keep out of reach of children. If swallowed, get medical help or contact Poison Control Center right away.

Directions

- Place enough product on hands to cover all surfaces. Rub hands together until dry.
- Supervise children under age 6 when using this product avoid swallowing.

Other information

- Store between 15-30°C (59-86F).
- Avoid freezing and excessive heat above 40°C (104F).

Inactive ingredients

Acrylates/c10-30 alkyl acrylate crosspolymer, aminomethyl propanol, chloroxylenol, glycerin, methyl gluceth-10, parfum, water.

Package Label/Principal Display Panel

NDC: 78692-134-34; 500 ml